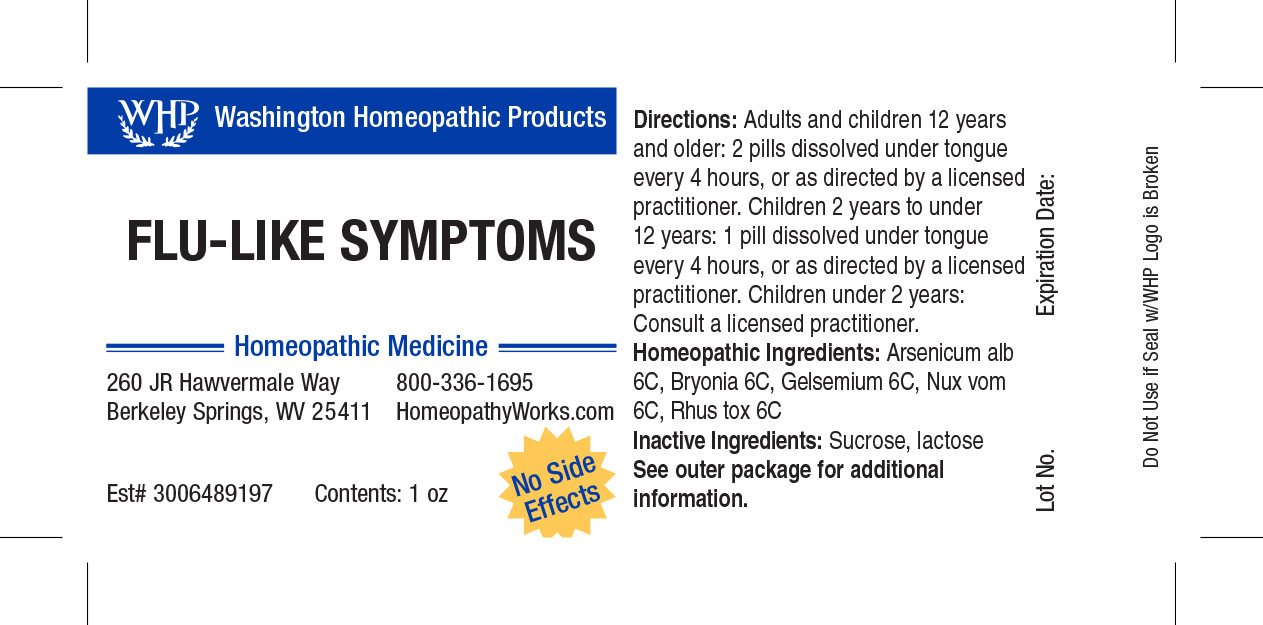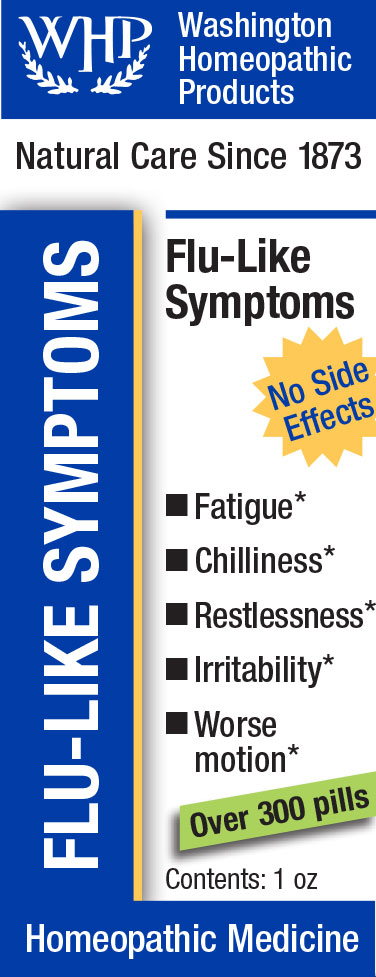 DRUG LABEL: WHP Flu like Symptoms
NDC: 71919-801 | Form: PELLET
Manufacturer: Washington Homeopathic Products
Category: homeopathic | Type: HUMAN OTC DRUG LABEL
Date: 20250128

ACTIVE INGREDIENTS: BRYONIA ALBA ROOT 6 [hp_C]/1 1; GELSEMIUM SEMPERVIRENS ROOT 6 [hp_C]/1 1; TOXICODENDRON PUBESCENS LEAF 6 [hp_C]/1 1; ARSENIC TRIOXIDE 6 [hp_C]/1 1; STRYCHNOS NUX-VOMICA SEED 6 [hp_C]/1 1
INACTIVE INGREDIENTS: SUCROSE; LACTOSE

WHP Flu-like Symptoms

ACTIVE INGREDIENTS

BRYONIA 6C

GELSEMIUM 6C

RHUS TOX 6C

ARSENICUM ALB 6C

NUX VOM 6C

USES

Temporarily relieves flu-like symptoms.

KEEP OUT OF REACH OF CHILDREN

As with all medications, keep out of reach of children.

INDICATIONS

BRYONIA Worse motion

GELSEMIUM Lethargy

RHUS TOX Better motion

ARSENICUM ALB Vomiting

NUX VOM Vomiting

STOP USE AND ASK DOCTOR

If symptoms persist or recur, discontinue use. If pregnant or nursing, consult a licensed practitioner before using this product.

DIRECTIONS

Directions: Adults and children 12 years and older: 2 pills dissolved under tongue every 4 hours, or as directed by a licensed practitioner. Children 4 years to under 12 years: 1 pill dissolved under tongue every 4 hours, or as directed by a licensed practitioner. Children under 4 years: Consult a licensed practitioner.

INACTIVE INGREDIENTS

Sucrose/Lactose